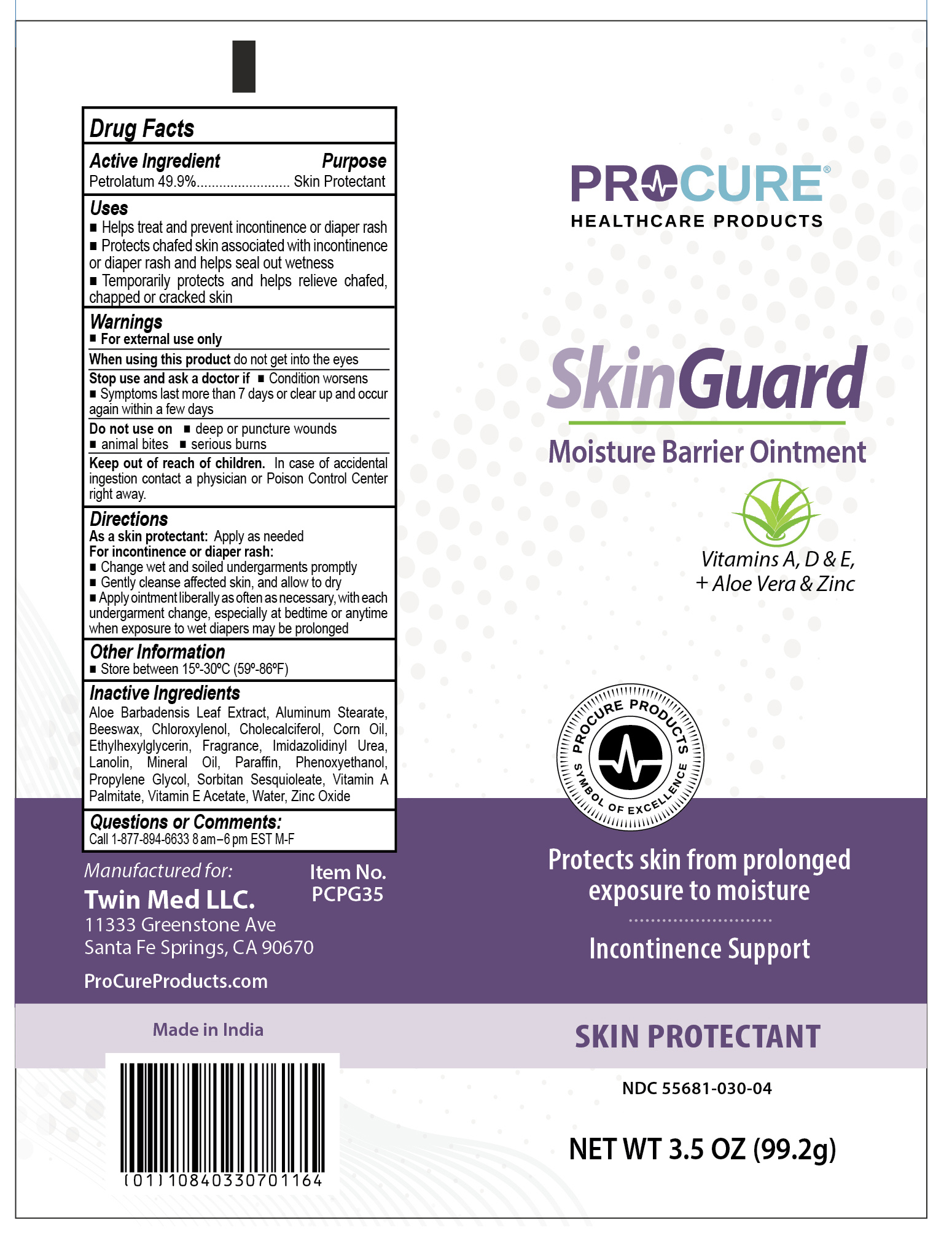 DRUG LABEL: ProCure SkinGuard
NDC: 55681-030 | Form: OINTMENT
Manufacturer: Twin Med LLC
Category: otc | Type: HUMAN OTC DRUG LABEL
Date: 20250725

ACTIVE INGREDIENTS: PETROLATUM 49.9 g/100 g
INACTIVE INGREDIENTS: LANOLIN; ALUMINUM STEARATE; CORN OIL; PHENOXYETHANOL; ALOE VERA LEAF; ZINC OXIDE; .ALPHA.-TOCOPHEROL ACETATE; SORBITAN SESQUIOLEATE; PARAFFIN; ETHYLHEXYLGLYCERIN; CHLOROXYLENOL; WATER; PROPYLENE GLYCOL; CHOLECALCIFEROL; VITAMIN A PALMITATE; IMIDUREA; YELLOW WAX; MINERAL OIL

Active Ingredient

Petrolatum 49.9%

Purpose

Skin Protectant

Uses

- Helps treat and prevent incontinence or diaper rash
- Protects chafed skin associated with incontinence or diaper rash and helps seal out wetness
- Temporarily protects and helps relieve chafed, chapped or cracked skin

Warnings

For External Use Only

When using this product do not get into the eyes

Stop use and ask a doctor if

- Condition worsens
- Symptoms last more than 7 days or clear up and occur again within a few days

Do not use on deep or puncture wounds, animal bites, or serious burns

Keep out of reach of children. In case of accidental ingestion contact a physician or Poison Control Center right away.

Directions

For skin protectant use: apply as needed
For incontinence or diaper rash:

- Change wet and soiled undergarments promptly
- Gently cleanse affected skin, and allow to dry
- Apply ointment liberally as often as necessary, with each undergarment change, especially at bedtime or anytime when exposure to wet diapers may be prolonged

Directions

For skin protectant use: apply as needed
For incontinence or diaper rash:

- Change wet and soiled undergarments promptly
- Gently cleanse affected skin, and allow to dry
- Apply ointment liberally as often as necessary, with each undergarment change, especially at bedtime or anytime when exposure to wet diapers may be prolonged

Inactive Ingredients

Mineral Oil, Water, Propylene Glycol, Paraffin, Zinc Oxide, Sorbitan Sesquioleate, Lanolin, Beeswax, Aluminum Stearate, Corn Oil, Phenoxyethanol, Ethylhexylglycerin, Fragrance, Imidazolidinyl Urea, Chloroxylenol, Aloe Barbadensis Leaf Extract, Cholecalciferol, Vitamin A Palmitate, Vitamin E Acetate